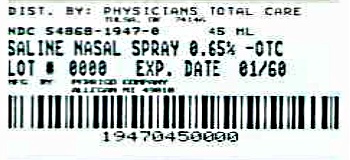 DRUG LABEL: Saline Nasal
NDC: 54868-1947 | Form: SPRAY
Manufacturer: Physicians Total Care, Inc.
Category: otc | Type: HUMAN OTC DRUG LABEL
Date: 20120712

ACTIVE INGREDIENTS: SODIUM CHLORIDE 6.5 mg/1 mL
INACTIVE INGREDIENTS: WATER; SODIUM PHOSPHATE, DIBASIC, DIHYDRATE; BENZYL ALCOHOL; SODIUM PHOSPHATE, MONOBASIC ANHYDROUS; BENZALKONIUM CHLORIDE

Saline Nasal Spray Drug Facts

Active ingredient

Sodium Chloride 0.65%

Uses

For dry nasal membranes squeeze twice in each nostril as needed.

Upright delivers a spray; Horizontally a stream; Upside down a drop.

Warnings

The use of this dispenser by more than one person may spread infection.

Directions

For dry nasal membranes squeeze twice in each nostril as needed.

Inactive ingredients

Purified Water, sodium chloride 0.65%, Disodium Phosphate, Phenylcarbinol, Monosodium Phosphate, Benzalkonium Chloride

Package/Label Principal Display Panel

NDC 54868-1947-0

Saline Nasal Spray - 0.65%

sodium chloride

45 mL